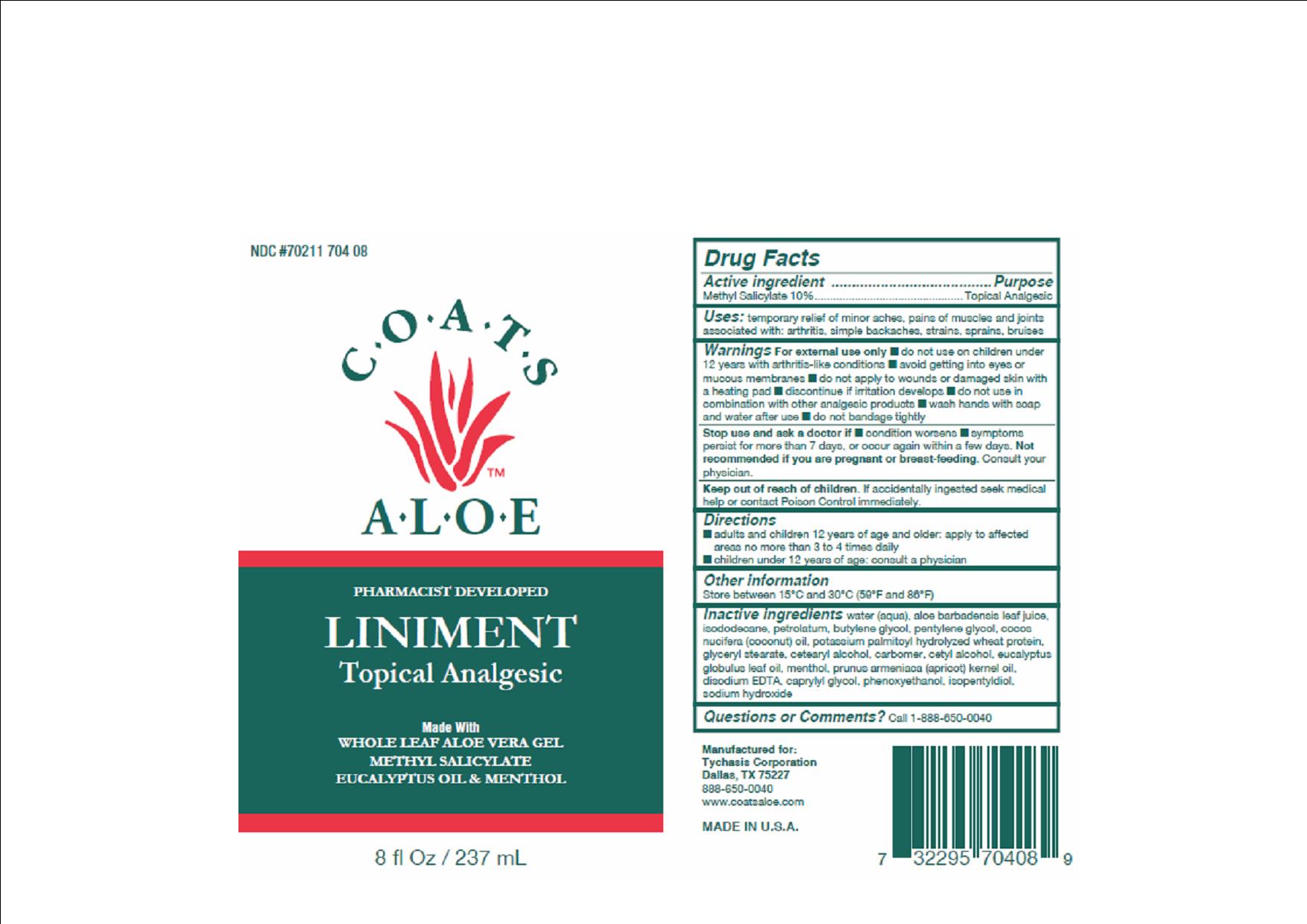 DRUG LABEL: COATS ALOE ANALGESIC
NDC: 70211-704 | Form: LOTION
Manufacturer: TYCHASIS CORPORATION
Category: otc | Type: HUMAN OTC DRUG LABEL
Date: 20241028

ACTIVE INGREDIENTS: METHYL SALICYLATE 10 g/100 mL
INACTIVE INGREDIENTS: ALOE VERA LEAF; PETROLATUM; BUTYLENE GLYCOL; PENTYLENE GLYCOL; COCONUT OIL; HYDROLYZED WHEAT PROTEIN (ENZYMATIC, 3000 MW); GLYCERYL STEARATE SE; CETYL ALCOHOL; EUCALYPTUS OIL; MENTHOL; APRICOT KERNEL OIL; CAPRYLYL GLYCOL; PHENOXYETHANOL; ISOPENTYLDIOL; WATER; SODIUM HYDROXIDE

COATS ALOE LINIMENT TOPICAL ANALGESIC

Active Ingredient:

Methyl Salicylate 10%

Purpose:

Topical analgesic, topical pain relief for intact skin.

Warnings:

- For external use only.
- Avoid contact with eyes or mucous membranes.
- Do not apply to wounds or damaged skin with a heating pad.
- Discontinue if irritation develops.
- Wash hands with soap and water after use.
- Do not banadage tightly.

Stop use if:

Stop use and ask a doctor if condition worsens, if symptoms persist more than 7 days, or if symptoms worsen within a few days.

Pregnant or breastfeeding:

Not recommended if you are pregnant or breastfeeding.

Consult your physician.

Indications and Usage:

Temporary relief of minor aches and pains of muscles and joints associated with:

- arthritis
- simple backaches
- strains
- sprains
- bruises

Do not use in combination with other topical analgesic products.

Keep out of reach of children:

If accidentally ingested, seek medical help or contact poison control immediately.

Directions:

Adults and children 12 years of age and older: Apply to affected areas no more than 3-4 times daily.

Children under 12 years of age: Consult a physician.

Other information:

Store between 15o C and 30o C (59o F and 86o F).

Inactive Ingredients:

aloe barbadenesis leaf juice, butylene glycol, caprylyl glycol, carbomer, cetearyl alcohol, cetyl alcohol, coconut oil, disodium EDTA, eucalyptus leaf oil, glyceryl stearate, isododecane, isopentylidiol, menthol, pentylene glycol, petrolatum, phenoxyethanol, potassium palmitol hydrolyzed wheat protein, apricot kernel oil, sodium hydroxide, water

Questions:

Toll free number 888-650-0040